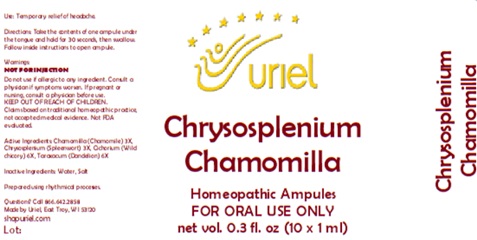 DRUG LABEL: Chrysosplenium Chamomilla
NDC: 48951-3088 | Form: LIQUID
Manufacturer: Uriel Pharmacy Inc.
Category: homeopathic | Type: HUMAN OTC DRUG LABEL
Date: 20260227

ACTIVE INGREDIENTS: MATRICARIA RECUTITA 3 [hp_X]/1 mL; CHRYSOSPLENETIN 3 [hp_X]/1 mL; CICHORIUM INTYBUS WHOLE 6 [hp_X]/1 mL; TARAXACUM PALUSTRE ROOT 6 [hp_X]/1 mL
INACTIVE INGREDIENTS: WATER; SODIUM CHLORIDE

Chrysosplenium Chamomilla

PURPOSE

Use: Temporary relief of headache.

INDICATIONS AND USAGE

FOR ORAL USE ONLY

DOSAGE AND ADMINISTRATION

Directions: Take the contents of one ampule under the tongue and hold for 30 seconds, then swallow. Follow inside instructions to open ampule.

Warnings:
NOT FOR INJECTION
Do not use if allergic to any ingredient. Consult a physician if symptoms worsen. If pregnant or nursing, consult a physician before use.
Claims based on traditional homeopathic practice, not accepted medical evidence. Not FDA evaluated.

KEEP OUT OF REACH OF CHILDREN.

ACTIVE INGREDIENT

Active Ingredients: Chamomilla (Chamomile) 3X, Chrysosplenium (Spleenwort) 3X, Cichorium (Wild chicory) 6X, Taraxacum (Dandelion) 6X

Inactive Ingredients: Water, Salt

Prepared using rhythmical processes.

QUESTIONS

Questions? Call 866.642.2858 Made by Uriel, East Troy, WI 53120 shopuriel.com

Lot: